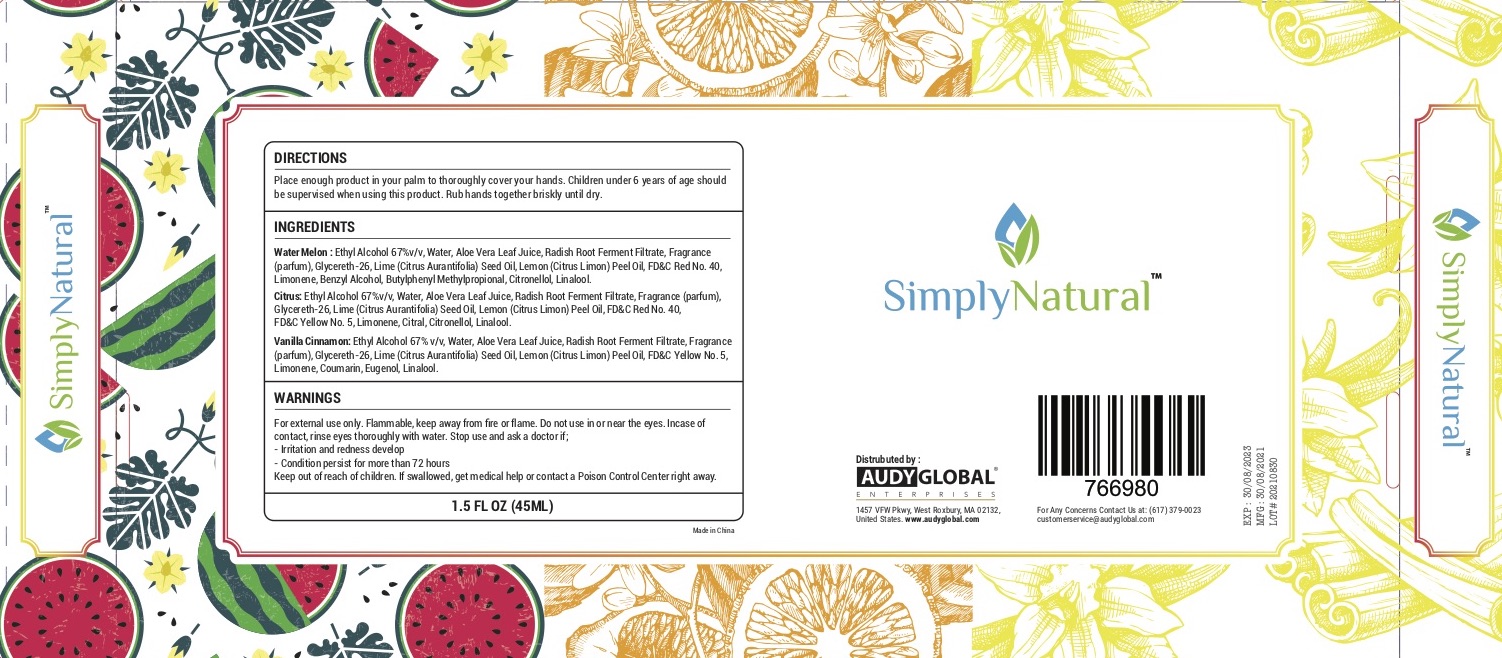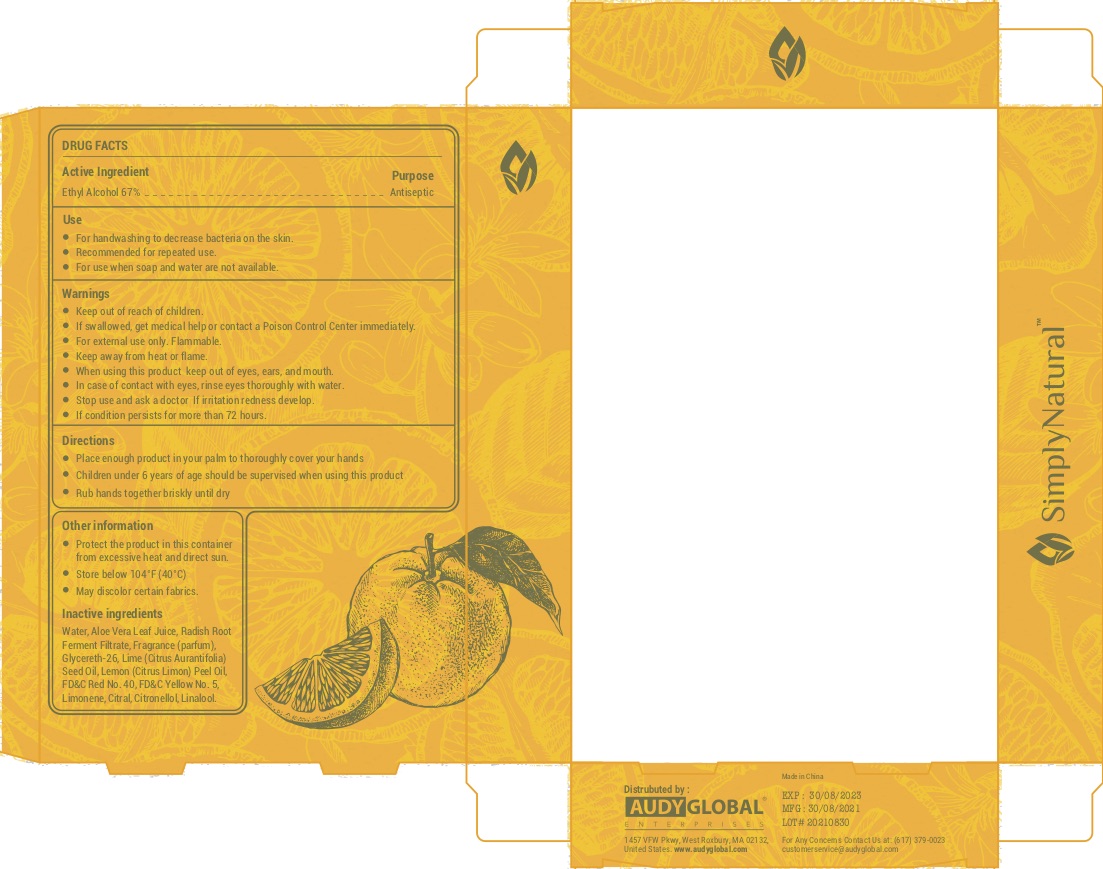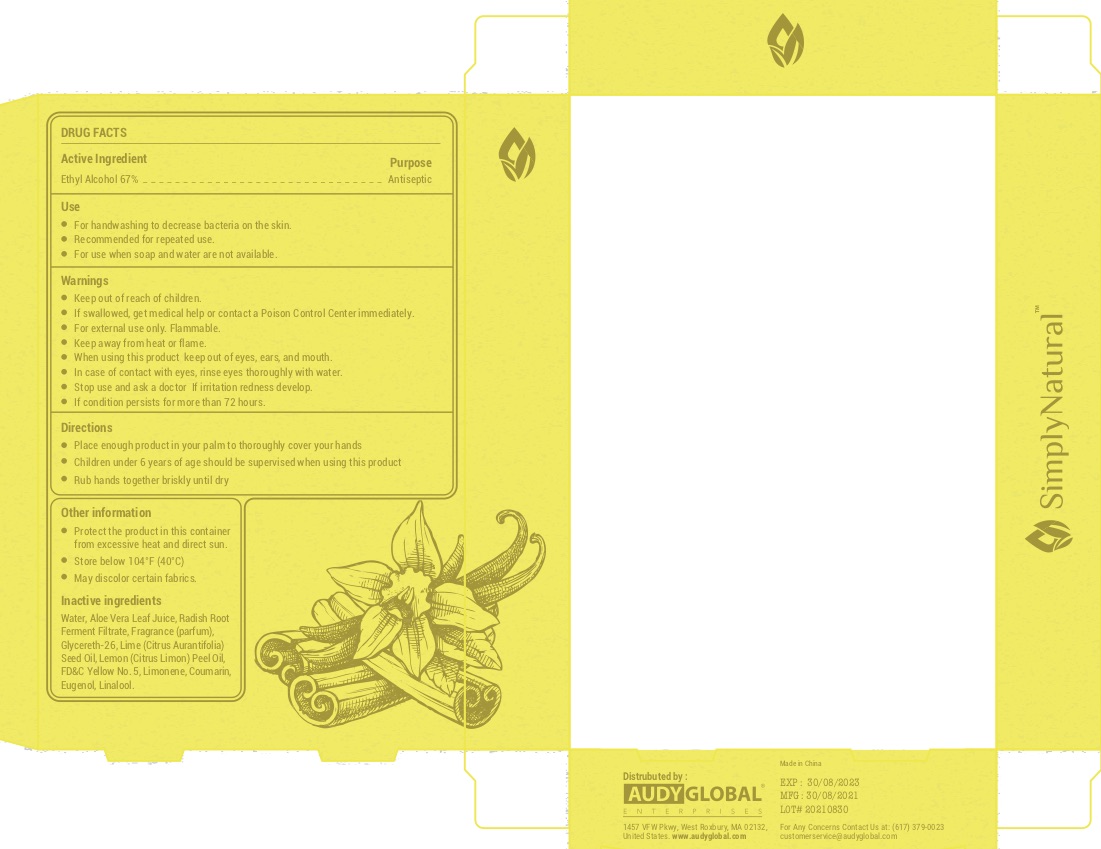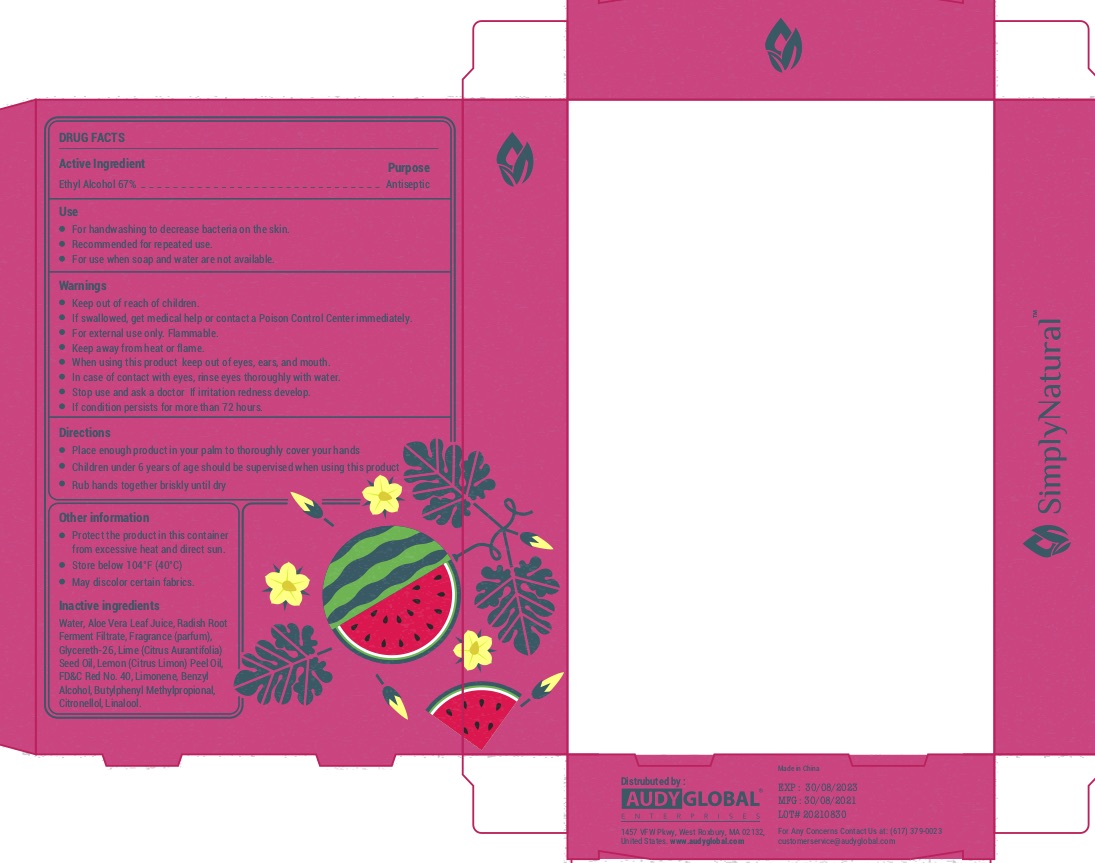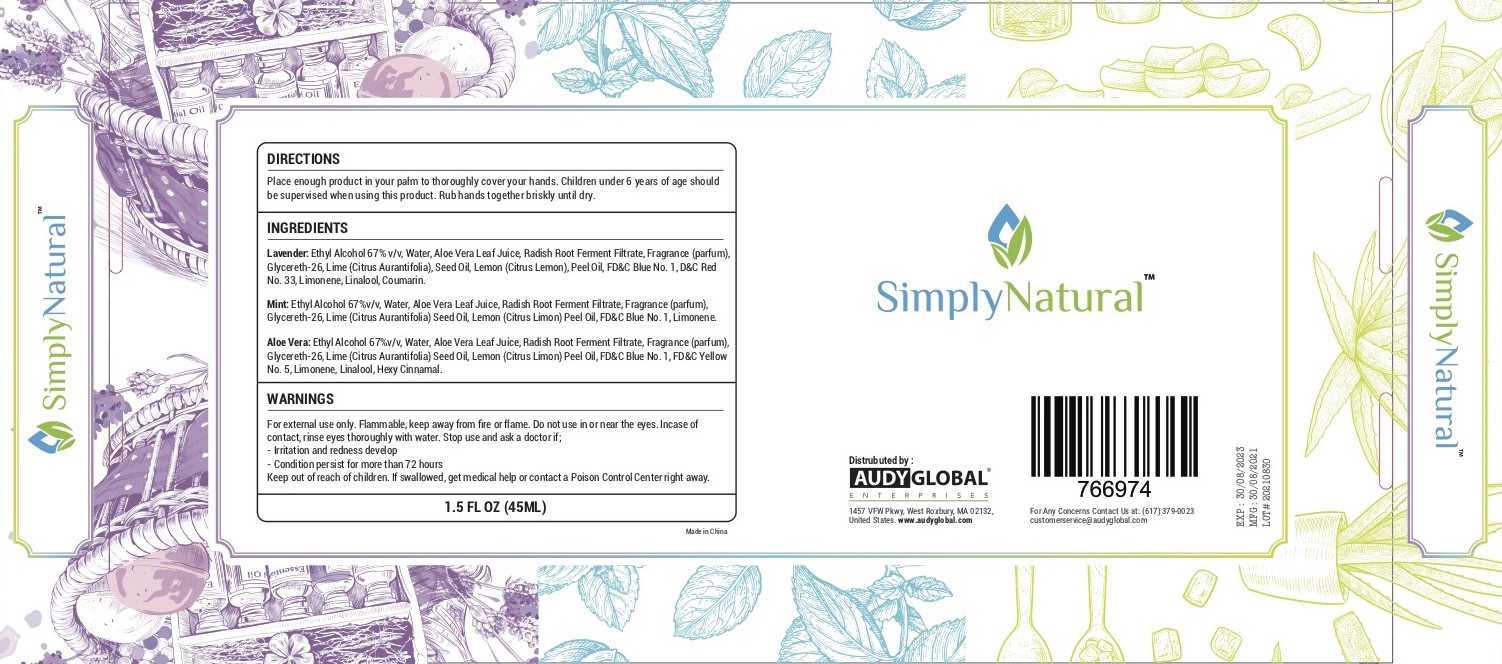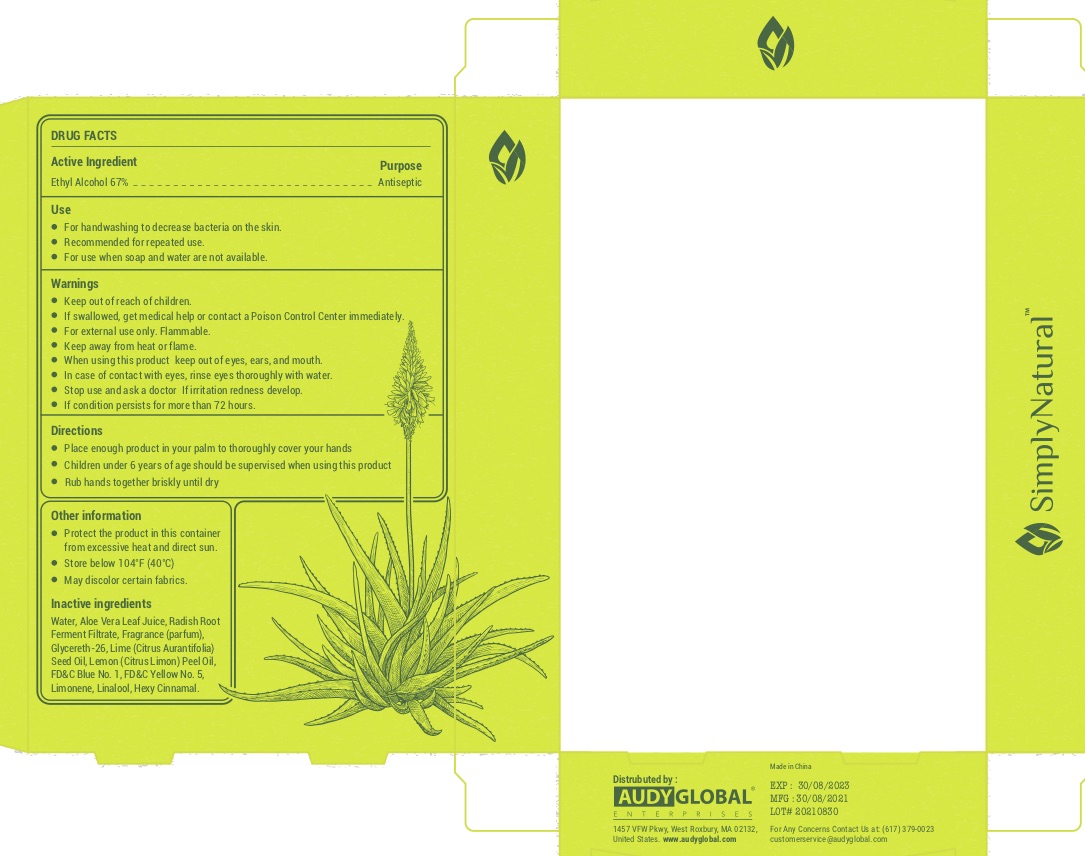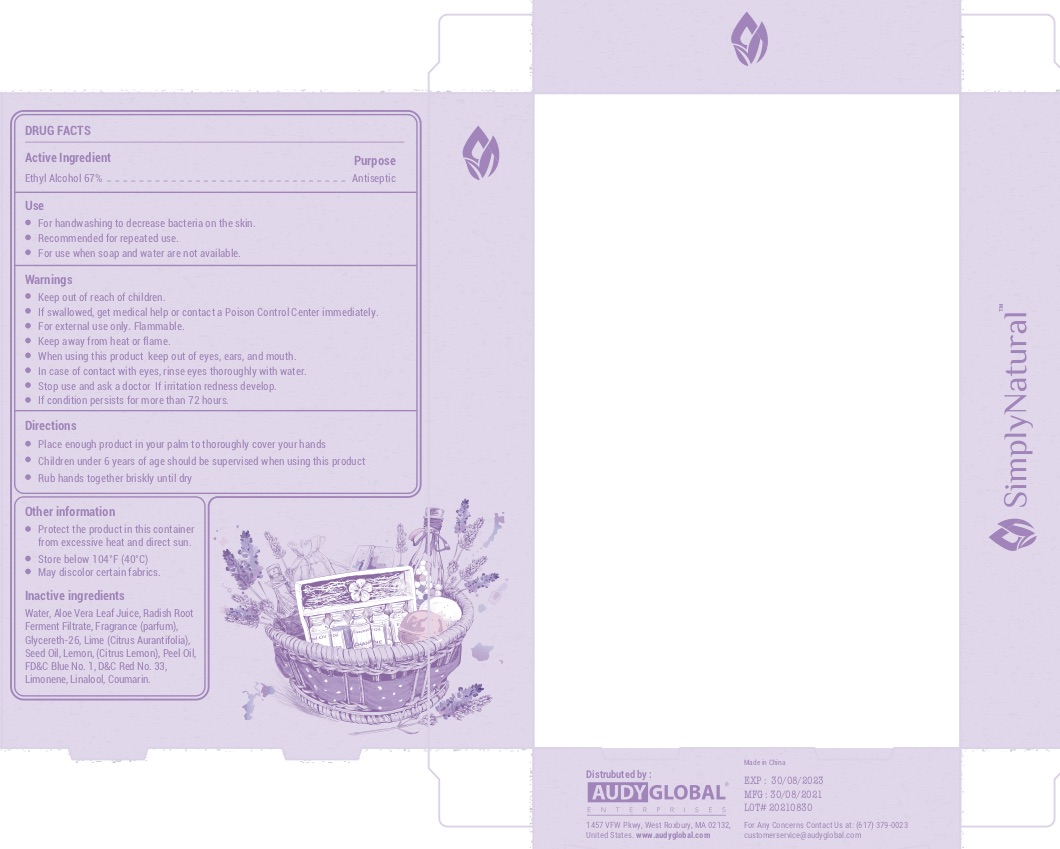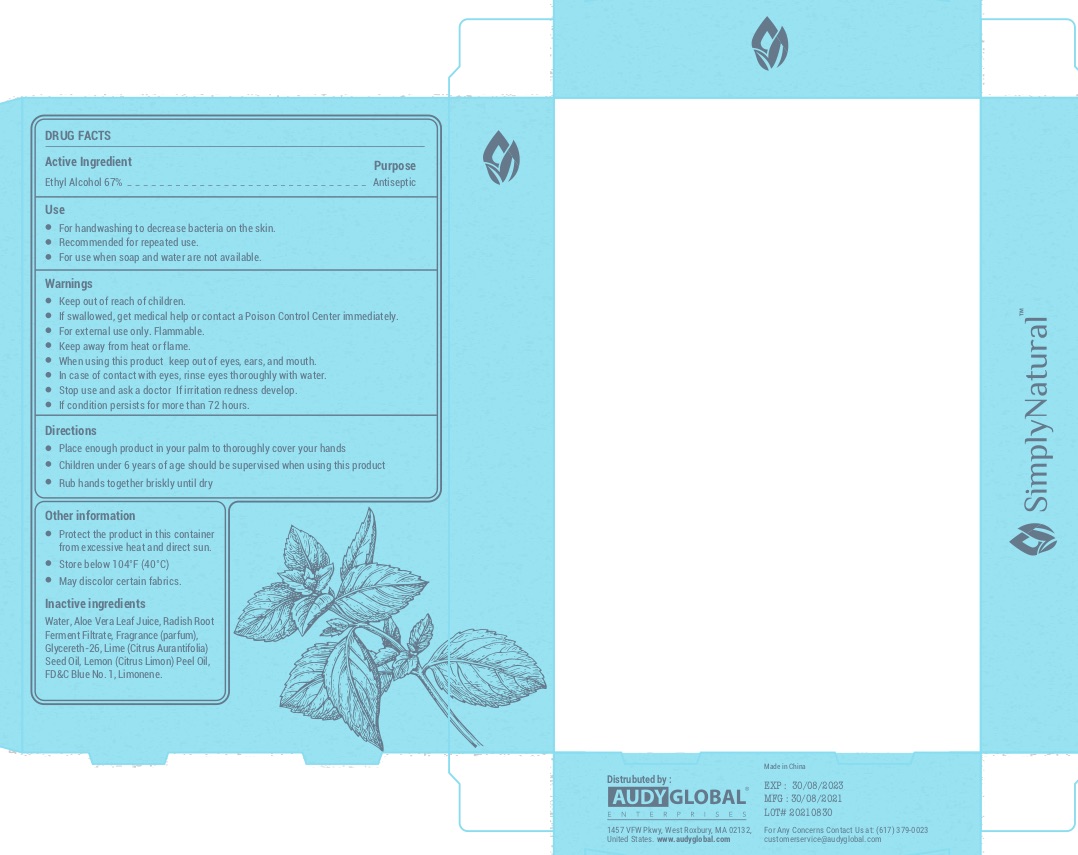 DRUG LABEL: Hand Sanitizer
NDC: 75778-006 | Form: GEL
Manufacturer: Audy Global Enterprises Inc.
Category: otc | Type: HUMAN OTC DRUG LABEL
Date: 20211025

ACTIVE INGREDIENTS: ALCOHOL 67 mL/100 mL
INACTIVE INGREDIENTS: LIMONENE, (+)-; ALOE VERA LEAF; LEUCONOSTOC/RADISH ROOT FERMENT FILTRATE; WATER; CITRUS AURANTIFOLIA SEED OIL; LEMON OIL, TERPENELESS; FD&C RED NO. 40; GLYCERETH-26; FD&C YELLOW NO. 5; CITRAL; .BETA.-CITRONELLOL, (R)-; LINALOOL, (+/-)-

Simply Natural Hand Sanitizer

Active Ingredient(s)

Ethyl Alcohol 67%

Purpose

Antiseptic

Use

For handwashing to decrease bacteria on the skin. Recommended for repeated use.

Warnings

For external use only. Flammable. Keep away from heat or flame.

Keep out of reach of children. If swallowed, get medical help or contact a Poison Control Center right away.

When using this product keep out of eyes, ears, and mouth. In case of contact with eyes, rinse eyes thoroughly with water.

Stop use and ask a doctor If irritation redness develop.

If condition persists for more than 72 hours.

Directions

- Place enough product in your palm to thoroughly cover your hands
- Children under 6 years of age should be supervised when using this product
- Rub hands together briskly until dry

Other information

- Protect the product in this container

from excessive heat and direct sun.

- Store below 104°F (40°C)
- May discolor certain fabrics.

Inactive ingredients

Water, Aloe Barbadensis Leaf Juice, Radish Root Ferment Filtrate, Fragrance (parfum), Glycereth-26, Lime (Citrus Aurantifolia) Seed Oil, Lemon (Citrus Limon) Peel Oil, FD&C Red No. 40, FD&C Yellow No. 5, Limonene, Citral, Citronellol, Linalool

Package Label - Principal Display Panel

Package combination of 3 bottles, each bottle contains 45 mL NDC: 75778-006-30

Bottle 1 of 3, Water Melon scent 45 mL NDC: 75778-006-30

Bottle 2 of 3, Citrus scent 45 mL NDC: 75778-006-30

Bottle 3 of 3, Vanilla Cinnamon scent 45 mL NDC: 75778-006-30

Package combination of 3 bottles, each bottle contains 45 mL NDC: 75778-006-31

Bottle 1 of 3, Lavender scent 45 mL NDC: 75778-006-31

Bottle 2 of 3, Mint scent 45 mL NDC: 75778-006-31

Bottle 3 of 3, Aloe Vera scent 45 mL NDC: 75778-006-31